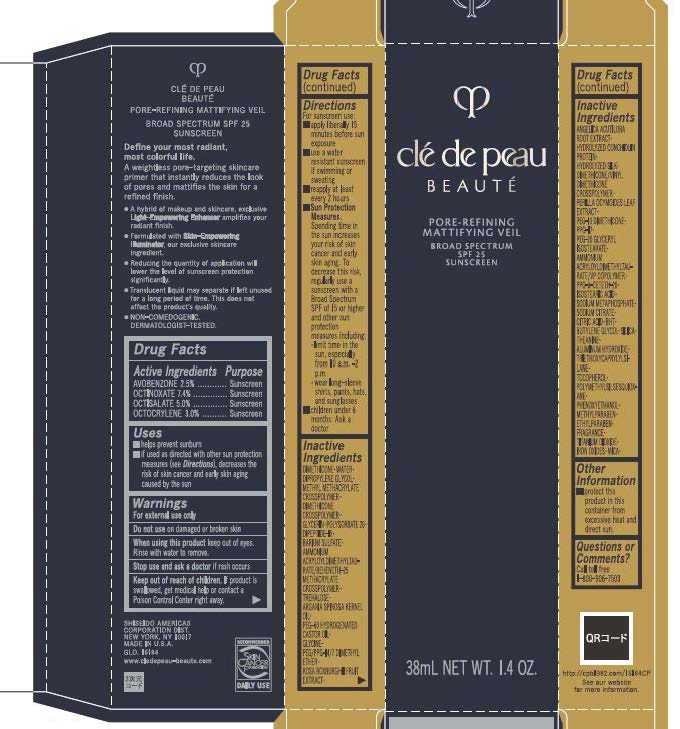 DRUG LABEL: cle de peau BEAUTE PORE-REFINING MATTIFYING VEIL
NDC: 58411-957 | Form: PASTE
Manufacturer: Shiseido Americas Corporation
Category: otc | Type: HUMAN OTC DRUG LABEL
Date: 20260204

ACTIVE INGREDIENTS: AVOBENZONE 0.9747 g/38 mL; OCTINOXATE 2.885112 g/38 mL; OCTISALATE 1.9494 g/38 mL; OCTOCRYLENE 1.16964 g/38 mL
INACTIVE INGREDIENTS: WATER; DIMETHICONE; DIPROPYLENE GLYCOL; DIMETHICONE CROSSPOLYMER; GLYCERIN; POLYSORBATE 20; DIPEPTIDE-15; BARIUM SULFATE; AMMONIUM ACRYLOYLDIMETHYLTAURATE/BEHENETH-25 METHACRYLATE CROSSPOLYMER (52000 MPA.S); TREHALOSE; ARGANIA SPINOSA KERNEL OIL; PEG-60 HYDROGENATED CASTOR OIL; GLYCINE; PEG/PPG-14/7 DIMETHYL ETHER; ROSA ROXBURGHII FRUIT; ANGELICA ACUTILOBA ROOT; DIMETHICONE/VINYL DIMETHICONE CROSSPOLYMER (SOFT PARTICLE); PERILLA FRUTESCENS LEAF; PEG-10 DIMETHICONE (600 CST); PPG-17; PEG-20 GLYCERYL ISOSTEARATE; AMMONIUM ACRYLOYLDIMETHYLTAURATE/VP COPOLYMER; PPG-8-CETETH-20; ISOSTEARIC ACID; SODIUM METAPHOSPHATE; SODIUM CITRATE; CITRIC ACID; BHT; BUTYLENE GLYCOL; SILICA; THEANINE; ALUMINUM HYDROXIDE; TRIETHOXYCAPRYLYLSILANE; TOCOPHEROL; POLYMETHYLSILSESQUIOXANE (4.5 MICRONS); PHENOXYETHANOL; METHYLPARABEN; ETHYLPARABEN; MICA; TITANIUM DIOXIDE; FERRIC OXIDE RED

cle de peau BEAUTE PORE-REFINING MATTIFYING VEIL

Drug Facts

Active Ingredients | Purpose
AVOBENZONE 2.5% | Sunscreen
OCTINOXATE 7.4% | Sunscreen
OCTISALATE 5% | Sunscreen
OCTOCRYLENE 3% | Sunscreen

Uses

- helps prevent sunburn
- if used as directed with other sun protection measures (see Directions), decreases the risk of skin cancer and early skin aging caused by the sun

Warnings

For external use only

Do not useon damaged or broken skin

WHEN USING

When using this productkeep out of eyes. Rinse with water to remove.

Stop use and ask a doctorif rash occurs

Keep out of reach of children. If product is swallowed, get medical help or contact a Poison Control Center right away.

Directions

- For sunscreen use:
- apply liberally 15 minutes before sun exposure
- use a water resistant sunscreen if swimming or sweating
- reapply at least every 2 hours
- Sun Protection Measures.Spending time in the sun increases your risk of skin cancer and early skin aging. To decrease this risk, regularly use a sunscreen with a broad spectrum SPF of 15 or higher and other sun protection measures including:
- limit time in the sun, especially from 10 a.m. - 2p.m.
- wear long-sleeve shirts, pant, hats, and sunglasses
- children under 6 months: Ask a doctor

INACTIVE INGREDIENT

WATER･DIMETHICONE･DIPROPYLENE GLYCOL･METHYL METHACRYLATE CROSS POLYMER･DIMETHICONE CROSSPOLYMER･GLYCERIN･POLYSORBATE 20･DIPEPTIDE-15･BARIUM SULFATE･AMMONIUM ACRYLOYLDIMETHYLTAURATE/BEHENETH-25 METHACRYLATE CROSSPOLYMER･TREHALOSE･ARGANIA SPINOSA KERNEL OIL･PEG-60 HYDROGENATED CASTOR OIL ･GLYCINE ･PEG/PPG-14/7 DIMETHYLE ETHER･ROSA ROXBURGHII FRUIT EXTRACT･ANGELICA ACUTILOBA ROOT EXTRACT･HYDROLYZED CONCHIOLIN PROTEIN･HYDRALIZED SILK･DIMETHICONE/VINYL DIMETHICONE CROSSPOLYMER･ PERILLA OCYMOIDES LEAF EXTRACT･PEG-10 DIMETHICONE･PPG-17･PEG-20 GLYCERYL ISOSTEARATE･AMMONIUM ACRYLOYLDIMETHYLTAU-RATE/VP COPOLYMER･PPG-8-CETETH-20･ISOSTEARIC ACID･SODIUM METAPHOSPHATE･SODIUM CITRATE･CITRIC ACID･BHT･BUTYLENE GLYCOL･SILICA･THEANINE･ALUMINUM HYDROXIDE ･TRIETHOXYCAPRYLYLSILANE･TOCOPHEROL ･POLYMETHYLSILSESQUIOXANE･ PHENOXYETHANOL･METHYLPARABEN･ETHYLPARABEN ･FRAGRANCE･IRON OXIDES･MICA･TITANIUM DIOXIDE･

Other Information

- protect this product in this container from excessive heat and direct sun.

Questions or Comments?

Call toll free 1-800-906-7503

PRINCIPAL DISPLAY PANEL- 38ml Tube

cle de peau BEAUTE

PORE-REFINING

MATTIFYING VEIL

BROAD SPECTRUM

SPF 25

SUNSCREEN

38mL NET WT. 1.4 OZ.